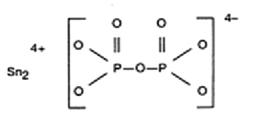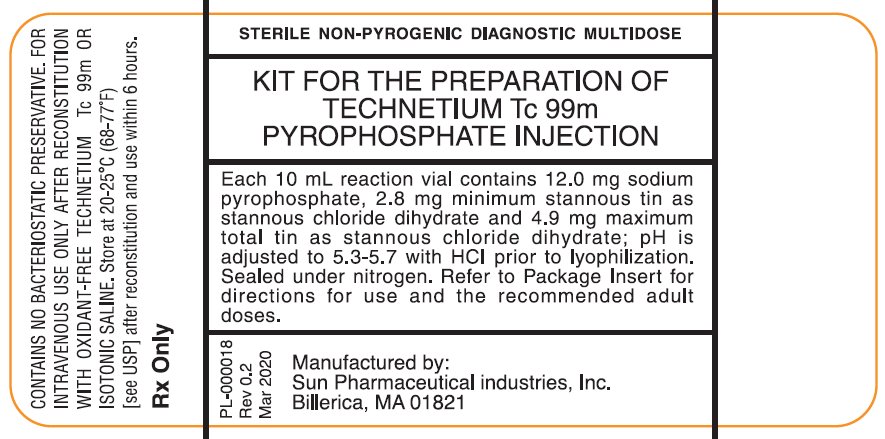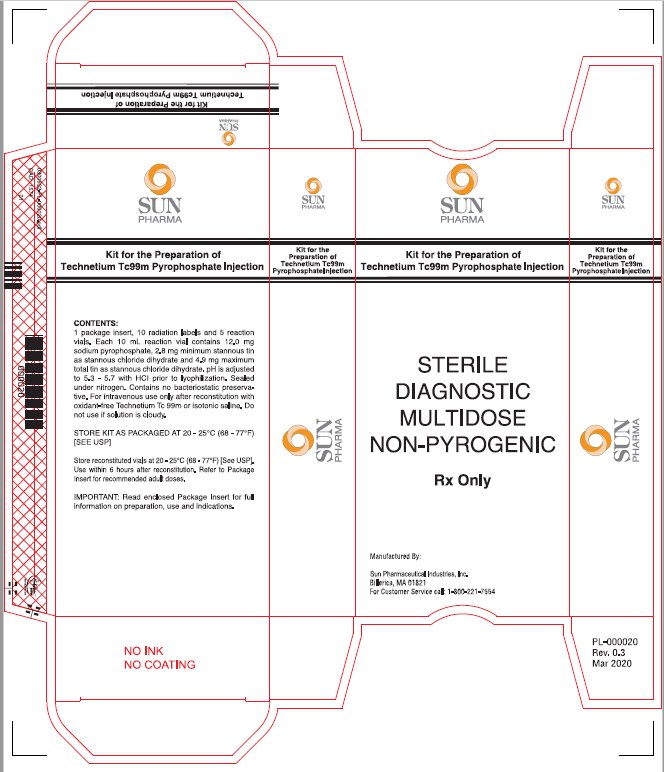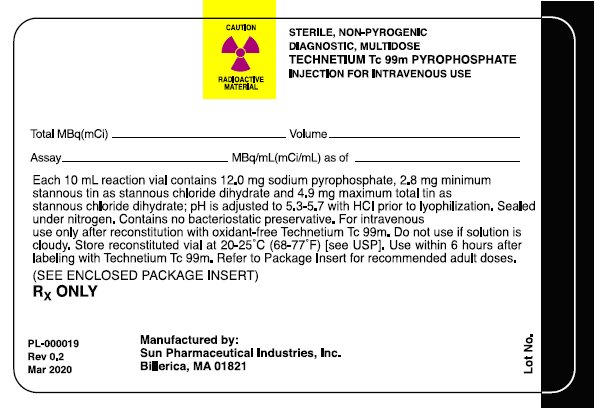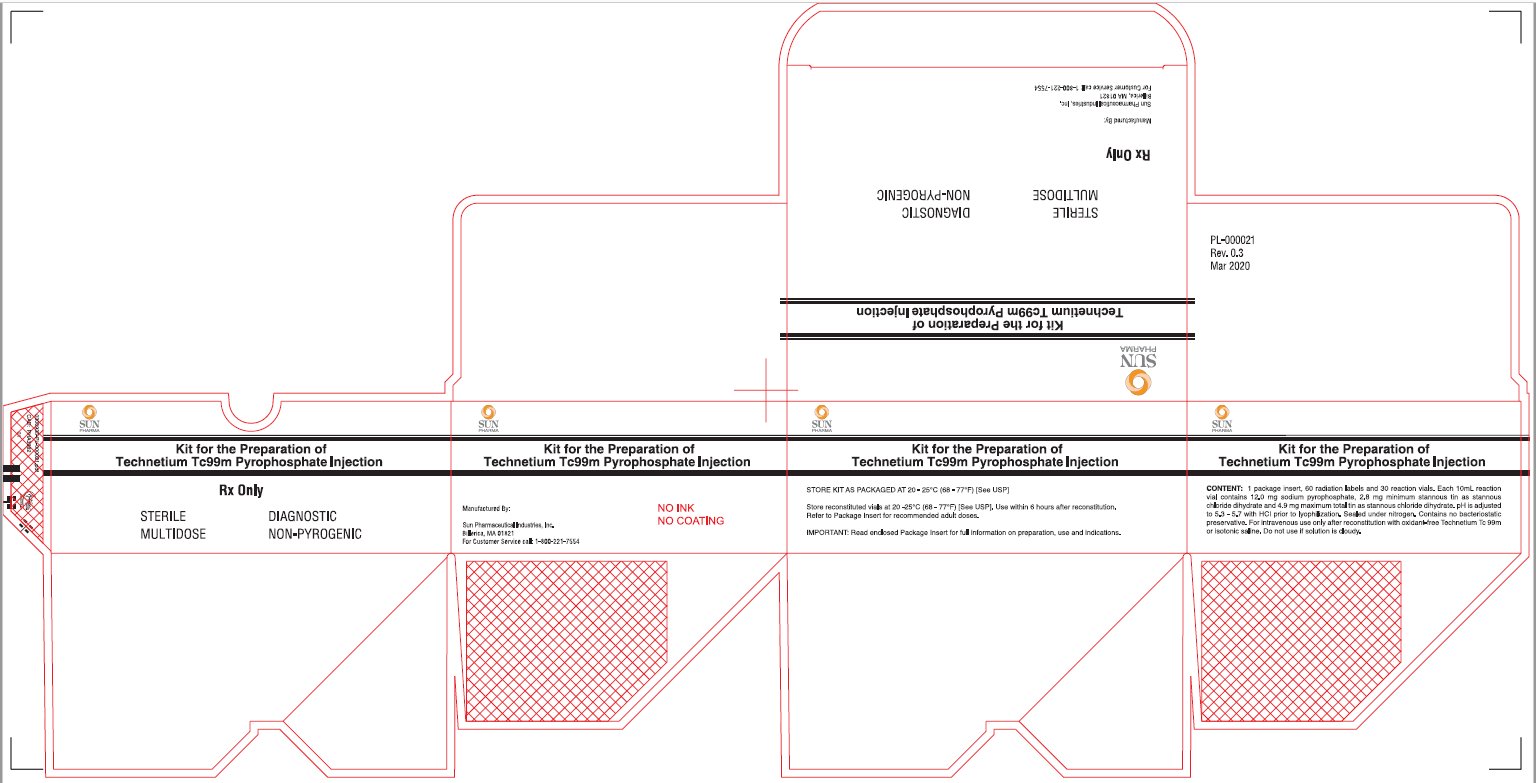 DRUG LABEL: Kit for the Preparation of Technetium Tc99m Pyrophosphate
NDC: 45567-0060 | Form: INJECTION
Manufacturer: Sun Pharmaceutical Industries, Inc.
Category: prescription | Type: HUMAN PRESCRIPTION DRUG LABEL
Date: 20250311

ACTIVE INGREDIENTS: TECHNETIUM TC-99M PYROPHOSPHATE 12 mg/10 mL
INACTIVE INGREDIENTS: STANNOUS CHLORIDE 2.8 mg/10 mL

Kit for the Preparation of
Technetium Tc 99m Pyrophosphate Injection
For Diagnostic Use
Rx Only

DESCRIPTION

Kit for the Preparation of Technetium Tc 99m Pyrophosphate Injection is a multidose reaction vial which contains the sterile, non-pyrogenic, non-radioactive ingredients necessary to produce Technetium Tc 99m Pyrophosphate Injection for diagnostic use by intravenous injection.

Each 10 mL vial contains 12.0 mg of sodium pyrophosphate, 2.8 mg minimum stannous tin as stannous chloride dihydrate and 4.9 mg maximum total tin as stannous chloride dihydrate; pH is adjusted to 5.3-5.7 with hydrochloric acid prior to lyophilization. No bacteriostatic preservative is present. Sealed under nitrogen.

The chemical names are: (1) Diphosphoric acid, Ditin (2^+) salt; (2) Ditin (2^+) pyrophosphate (4^-). The structural formula is:

When a solution of sterile, non-pyrogenic, oxidant-free isotonic Sodium Pertechnetate Tc 99m Injection U.S.P. is added to the vial, Technetium Tc 99m Pyrophosphate Injection is formed for intravenous injection.

When a solution of sterile, non-pyrogenic, isotonic saline is added to the vial, it forms
a blood pool imaging agent when Sodium Pertechnetate Tc 99m Injection is injected intravenously 30 minutes after the intravenous administration of the non-radioactive reconstituted Kit for the Preparation of Technetium Tc 99m Pyrophosphate Injection. The precise structure of Technetium Tc 99m Pyrophosphate Injection is not known at this time.

Physical Characteristics

Technetium Tc 99m decays by isomeric transition with a physical half-life of 6.02 hours.¹ The principal photon that is useful for detection and imaging studies is listed in Table 1.

TABLE 1: Principal Radiation Emission Data
Radiation | Mean Percent Per Disintegration | Mean Energy (keV)
Gamma-2 | 89.07 | 140.5

¹Kocher DC: Radioactive decay data tables. DOE/TIC-11026:108, 1981

External Radiation

The specific gamma ray constant for Tc 99m is 0.78 R/hr-millicurie at 1 cm. The first half-value layer is 0.017 cm of lead (Pb). A range of values for the relative attenuation of the radiation emitted by this radionuclide that results from interposition of various thicknesses of Pb is shown in Table 2. For example, the use of a 0.25 cm thickness of Pb will attenuate the radiation emitted by a factor of about 1,000.

TABLE 2: Radiation Attenuation by Lead Shielding
Shield Thickness (Pb) cm | Coefficient of Attenuation
0.017 | 0.5
0.08 | 10^-1
0.16 | 10^-2
0.25 | 10^-3
0.33 | 10^-4

To correct for physical decay of this radionuclide, the fractions that remain at selected intervals after the time of calibration are shown in Table 3.

TABLE 3: Physical Decay Chart: Tc 99m, half-life 6.02 hours
Hours | Fraction Remaining | Hours | Fraction Remaining
0* | 1.000 | 7 | 0.447
1 | 0.891 | 8 | 0.398
2 | 0.794 | 9 | 0.355
3 | 0.708 | 10 | 0.316
4 | 0.631 | 11 | 0.282
5 | 0.562 | 12 | 0.251
6 | 0.501

* Calibration time

CLINICAL PHARMACOLOGY

When injected intravenously, Technetium Tc 99m Pyrophosphate Injection has a specific affinity for areas of osteogenesis. It is also concentrated in the injured myocardium, primarily in areas of irreversibly damaged myocardial cells.

One to two hours after intravenous injection of Technetium Tc 99m Pyrophosphate Injection, an estimated 40 to 50 percent of the injected dose has been taken up by the skeleton, and approximately 0.01 to 0.02 percent per gram of acutely infarcted myocardium. Within a period of one hour, 10 to 11 percent remains in the vascular system, declining to approximately 2 to 3 percent twenty-four hours post injection.

The average urinary excretion was observed to be about 40 percent of the administered dose after 24 hours.

The non-radioactive reconstituted Kit for the Preparation of Technetium Tc 99m Pyrophosphate Injection also has an affinity for red blood cells. When administered 30 minutes prior to the intravenous administration of Sodium Pertechnetate Tc 99m Injection, approximately 76 percent of the injected activity remains in the blood pool providing excellent images of the cardiac chambers.

INDICATIONS AND USAGE

Technetium Tc 99m Pyrophosphate Injection is a bone imaging agent used to demonstrate areas of altered osteogenesis, and a cardiac imaging agent used as an adjunct in the diagnosis of acute myocardial infarction.

Kit for the Preparation of Technetium Tc 99m Pyrophosphate Injection is a blood pool imaging agent which may be used for gated blood pool imaging and for the detection of sites of gastrointestinal bleeding. When reconstituted with sterile non-pyrogenic isotonic saline and administered intravenously 30 minutes prior to the intravenous administration of Sodium Pertechnetate Tc 99m Injection, approximately 76% of the injected radioactivity remains in the blood pool.

CONTRAINDICATIONS

None known.

WARNINGS

As an adjunct in the diagnosis of confirmed myocardial infarction (ECG and serum enzymes positive), the incidence of false negative images has been found to be 6 percent. False negative images can also occur if made prior to 24 hours in the evolutionary phase of the infarct or after 6 days in the resolution phase. In a limited study involving 22 patients in whom the ECG was positive and serum enzymes questionable or negative, but in whom the final diagnosis of acute myocardial infarction was made, the incidence of false negative images was 23 percent. The incidence of false positive images has been found to be 7 to 9 percent. False positive images have also been reported following coronary by-pass graft surgery, in unstable angina pectoris, old myocardial infarcts and in cardiac contusions.

Preliminary reports indicate impairment of brain scans using Sodium Pertechnetate Tc99m Injection which have been preceded by a bone scan using an agent containing stannous ions. The impairment may result in false positive or false negative brain scans. It is recommended, where feasible, that brain scans precede bone imaging procedures. Alternately, a brain imaging agent such as Technetium Tc 99m Pentetate Injection may be employed.

The biodistribution of technetium Tc 99m pyrophosphate may be altered in the presence of high levels of certain cations (iron, calcium, and aluminum). This may result in reduced uptake of radionuclide in the skeleton and increased extraosseal uptake, which may potentially degrade imaging quality. High levels of these cations may be caused by concomitant medications or medical conditions (e.g., iron overload, hypercalcemia, etc.). Most cases were observed after iron infusion. (See PRECAUTIONS, Drug Interactions.)

PRECAUTIONS

General

The lyophilized contents of the Kit for the Preparation of Technetium Tc 99m Pyrophosphate Injection reaction vial are to be administered to the patient only as an intravenous solution (see Procedures for Reconstitution). Any Sodium Pertechnetate Tc 99m solution which contains an oxidizing agent is not suitable for use with Kit for the Preparation of Technetium Tc 99m Pyrophosphate Injection. When reconstituted with Sodium Pertechnetate Tc 99m, Technetium Tc 99m Pyrophosphate Injection must be used within 6 hours. Kit for the Preparation of Technetium Tc 99m Pyrophosphate Injection may also be reconstituted with sterile, non-pyrogenic isotonic saline containing no preservatives and injected intravenously prior to the administration of Sodium Pertechnetate Tc 99m Injection.

Kit for the Preparation of Technetium Tc 99m Pyrophosphate Injection contains no preservatives.

Vials are sealed under nitrogen: air or oxygen is harmful to the contents of the vials and the vials should not be vented.

The components of the Kit for the Preparation of Technetium Tc 99m Pyrophosphate Injection are supplied sterile and non-pyrogenic. Aseptic procedures normally employed in making additions and withdrawals for sterile, non-pyrogenic containers should be used during addition of the Sodium Pertechnetate Tc 99m Injection and the withdrawal of doses for patient administration.

Shielding should be utilized when preparing Technetium Tc 99m Pyrophosphate Injection.

Technetium Tc 99m Pyrophosphate Injection as well as other radioactive drugs must be handled with care, and appropriate safety measures should be used to minimize radiation exposure to the patients and clinical personnel consistent with proper patient management.

The solution should not be used if cloudy, discolored, or found to contain particulate matter.

Radiopharmaceuticals should be used only by physicians who are qualified by training and experience in the safe use and handling of radionuclides, and whose experience and training have been approved by the appropriate government agency authorized to license the use of radionuclides.

No special handling is required for the non-radioactive drug product.

Bone Imaging

Both prior to and following Technetium Tc 99m Pyrophosphate Injection administration, if not contraindicated for the patient’s cardiac condition, patients should be encouraged to drink fluids. Patients should void as often as possible after the Technetium Tc 99m Pyrophosphate Injection to minimize background interference and unnecessary radiation exposure from accumulation in the bladder.

Cardiac Imaging

Patient’s cardiac condition should be stable before beginning the cardiac imaging procedure.

Interference from chest wall lesions such as breast tumors and healing rib fractures can be minimized by employing the three recommended projections. (See DOSAGE AND ADMINISTRATION). False-positive and false-negative myocardial scans may occur; therefore, the diagnosis of acute myocardial infarction depends on the overall assessment of laboratory and clinical findings.

Blood Pool Imaging

The non-radioactive reconstituted agent should be injected by direct venipuncture. Heparinized catheter systems should be avoided, as interference with red blood cell tagging will result. Cardiac pool imaging should be initiated 15 to 30 minutes after the administration of Sodium Pertechnetate Tc 99m Injection.

The imaging of gastrointestinal bleeding is dependent on such factors as the region of imaging, rate and volume of the bleed, efficacy of the labeling of the red blood cells and timeliness of imaging. Due to these factors, images should be taken sequentially over a period of time until a positive image is obtained or clinical conditions warrant the discontinuance of the procedure. The period of time for collecting the images may range up to 36 hours.

Technetium Tc 99m Pyrophosphate Injection and the non-radioactive reconstituted Kit for the Preparation of Technetium Tc 99m Pyrophosphate Injection should be formulated within six (6) hours prior to clinical use.

Drug Interactions

The biodistribution of technetium Tc 99m pyrophosphate may be altered in the presence of high levels of certain cations (iron, calcium, and aluminum). This may result in reduced uptake of radionuclide in the skeleton and increased extraosseal uptake, which may potentially degrade imaging quality. In patients with high levels of these cations caused by concomitant medications, particularly patients receiving iron infusions, consider performing an imaging study with technetium Tc 99m pyrophosphate injection once the cation levels have normalized (e.g., after 3 to 5 half-lives of the cation). (See WARNINGS.)

Carcinogenesis, Mutagenesis, Impairment of Fertility

No long-term animal studies have been performed to evaluate carcinogenic potential or whether Technetium Tc 99m Pyrophosphate Injection affects fertility in males or females. Mutagenesis studies have not been conducted.

Pregnancy

Animal reproduction and teratogenicity studies have not been conducted with Technetium Tc 99m Pyrophosphate Injection. It is also not known whether Technetium Tc 99 Pyrophosphate Injection can cause fetal harm when administered to a pregnant woman or can affect reproductive capacity. Technetium Tc 99m Pyrophosphate Injection should be given to a pregnant woman only if clearly needed.

Ideally, examinations using radiopharmaceuticals, especially those elective in nature, to a woman of childbearing capability should be performed during the first few (approximately 10) days following the onset of menses.

Nursing mothers

Technetium Tc 99m Pyrophosphate Injection is excreted in human milk during lactation, therefore, formula feeding should be substituted for breast feeding.

Pediatric use

Safety and effectiveness in pediatric patients have not been established.

Geriatric use

Clinical studies of the Kit for the Preparation of Technetium Tc 99m Pyrophosphate Injection did not include sufficient numbers of subjects aged 65 and over to determine whether they respond differently from younger subjects. Other reported clinical experience has not identified differences in responses between the elderly and younger patients. In general, dose selection for an elderly patient should be cautious, usually starting at the low end of the dosing range, reflecting the greater frequency of decreased hepatic, renal, or cardiac function, and of concomitant disease or other drug therapy.

This drug is known to be substantially excreted by the kidney, and the risk of toxic reactions to this drug may be greater in patients with impaired renal function. Because elderly patients are more likely to have decreased renal function, care should be taken in dose selection, and it may be useful to monitor renal function.

ADVERSE REACTIONS

Some hypersensitivity reactions have been associated with pyrophosphate use.

DOSAGE AND ADMINISTRATION

After preparation with oxidant-free Sodium Pertechnetate Tc 99m Injection, the suggested dose range of Technetium Tc 99m Pyrophosphate Injection in the average ADULT patient (70 kg) is:

Bone Imaging -185-555 megabecquerels (5-15 mCi)

Cardiac Imaging -370-555 megabecquerels (10-15 mCi)

The suggested dose range of the non-radioactive reconstituted Kit for the Preparation of Technetium Tc 99m Pyrophosphate Injection in the average ADULT patient (70 kg) is:

Blood Imaging -Administer not less than one-third nor more than the total contents of one vial

[555 -740 megabecquerels (15-20mCi) of Pertechnetate Tc 99m Injection].

Bone and Cardiac Imaging

Technetium Tc 99m Pyrophosphate Injection is injected intravenously over a 10 to 20 second period. For optimal results, bone imaging should be done 1 to 6 hours following administration. Cardiac imaging should be done 30 to 90 minutes following administration. The acute myocardial infarct can be visualized from 24 hours to 6 days following onset of symptoms, with maximum localization at 48 to 72 hours. Cardiac imaging should be done with a gamma scintillation camera. It is recommended that images be made of the anterior, left anterior oblique and left lateral projections.

Blood Pool Imaging

Kit for the Preparation of Technetium Tc 99m Pyrophosphate Injection may be reconstituted with sterile, non-pyrogenic isotonic saline containing no preservatives. Administer not less than one-third nor more than the total contents of one vial 30 minutes prior to the intravenous administration of 555 to 740 megabecquerels (15-20 mCi) Sodium Pertechnetate Tc 99m Injection. The non-radioactive reconstituted Kit for the Preparation of Technetium Tc 99m Pyrophosphate Injection should be injected by direct venipuncture. Heparinized catheter systems should be avoided. Cardiac imaging should be done 10 to 30 minutes following the administration of Sodium Pertechnetate Tc 99m Injection utilizing a scintillation camera interfaced to an electrocardiographic gating device.

Parenteral drug products should be inspected visually for particulate matter and discoloration prior to administration whenever solution and container permit.

The patient dose should be measured by a suitable radioactivity calibration system immediately prior to administration.

Radiation Dosimetry

Bone and Cardiac Imaging

The effective half-life was assumed to be the physical half-life for all calculated values. The estimated radiation absorbed doses to an average ADULT patient (70 kg) from an intravenous injection of a maximum of 555 megabecquerels (15 mCi) of Technetium Tc 99m Pyrophosphate Injection are shown in Table 4.

TABLE 4: Estimated Absorbed Radiation Doses Bone and Cardiac Imaging*
 | Technetium Tc 99m Pyrophosphate Injection
Target Organ | mGy/555 MBq | rads/15 mCi
Total Body | 1.8 | 0.18
Kidneys | 3.6 | 0.36
Red Marrow | 3.5 | 0.35
Bone Surfaces | 21.1 | 2.11
Bladder Wall | 13.3 | 1.33
Testes | 1.4 | 0.14
Ovaries | 2.1 | 0.21
Effective Dose Equivalent | 3.3 mSv | 0.33 rem

*Based on the model in MIRD Dose Estimate Report No. 13 (J Nucl Med 30:1117-1122, 1989).

Estimate calculated using phantoms of Cristy & Eckerman (Report ORNL/TM-8381/V1 & V7). Bone and marrow model of Eckerman (Aspects of dosimetry of radionuclides within the skeleton with particular emphasis on the active marrow. In Fourth International Radiopharmaceutical Dosimetry Symposium; A.T. Schlafke-Stelson and E.E. Watson eds. CONF-851113, Oak Ridge Associated Universities, Oak Ridge, TN 37831, 1986. pp 514-534.) used.

The effective dose equivalent is a quantity which may be suitable for comparing risks of different procedures in nuclear medicine, radiology, and other applications involving ionizing radiation, but should not be construed to give information about risks to individual patients and should not be applied to situations involving radiation therapy.

Blood Pool Imaging

The estimated absorbed radiation doses to an average adult patient (70 kg) from an intravenous injection of 740 megabecquerels (20 mCi) of Sodium Pertechnetate Tc 99m Injection, 30 minutes after the intravenous administration of the non-radioactive reconstituted Kit for the Preparation of Technetium Tc 99m Pyrophosphate Injection are shown in Table 5.

TABLE 5: Estimated Absorbed Radiation Doses Blood Pool Imaginga
 | Sodium Pertechnetate Tc 99m 30 min.
 | Post Injection with Pyrophosphate
Target Organ | mGy/740 MBq | rads/20 mCi
Total Body | 3.2 | 0.32
Spleen | 3.6 | 0.36
Bladder Wallb | 24.0 | 2.40
Testes | 2.4 | 0.24
Ovaries | 4.6 | 0.46
Blood | 10.4 | 1.04
Red Marrow | 4.4 | 0.44

aAssume 75% of the Sodium Pertechnetate Tc 99m labels red blood cells and the other 25% remains as pertechnetate. Method of calculation: MIRD Dose Estimate Report No. 8, J Nucl Med. 17: 74-77, 1976.

bIf 25% excreted with 1 hour Tb

HOW SUPPLIED

The Kit for the Preparation of Technetium Tc 99m Pyrophosphate Injectionis supplied in packages of 5 or 30 sterile, non-pyrogenic, white capped 10mL vials.
Each multidose vial contains 12.0 mg sodium pyrophosphate, 2.8 mg minimum stannous tin as stannous chloride dihydrate and 4.9 mg maximum total tin as stannous chloride dihydrate; pH is adjusted with hydrochloric acid to 5.3-5.7 prior to lyophilization. No bacteriostatic preservative is present. Sealed under nitrogen.

Included in each 5-vial package are one package insert and 10 radiation labels.

Included in each 30-vial package are one package insert and 60 radiation labels.

Store the kit as packaged at 20-25°C (68-77°F) [See USP]. Store the reconstituted vials at 20-25°C (68-77°) [See USP].

Bone and Cardiac Imaging

Technetium Tc 99m Pyrophosphate Injection is prepared from Kit for the Preparation of Technetium Tc 99m Pyrophosphate Injection by the following aseptic procedure:

1. Waterproof gloves should be worn during the preparation procedure. Remove the white flip-off cap from the vial and swab the top of the vial closure with alcohol to sterilize the surface.
2. Complete the radiation label and affix to the vial. Place the vial in an appropriate radiation shield suitably labeled and identified.
3. With a sterile shielded syringe, aseptically obtain 1-10 milliliters of a suitable, oxidant free, sterile and non-pyrogenic Sodium Pertechnetate Tc 99m Injection containing no more than 3.7 gigabecquerels (100 mCi). Aseptically add the Sodium Pertechnetate Tc 99m Injection to the vial.
4. Swirl the contents of the vial for one minute and let stand for at least 10 minutes.
5. Record date and time of preparation.
6. It is recommended that the radiochemical purity of the prepared radiopharmaceutical be checked prior to patient administration.
7. Examine vial contents for particulates and discoloration prior to injection.
8. Withdrawals for administration must be made aseptically using a sterile shielded syringe and needle. Since the vials contain nitrogen to prevent oxidation of the complex, the vials should not be vented. If repeated withdrawals are made from a vial, the replacement of contents with air should be minimized.
9. Aseptically withdraw material with a sterile lead shielded syringe for use within six (6) hours of preparation. For optimal results, this time should be minimized. The vial contains no bacteriostatic preservative. Store the reconstituted vial at 20-25°C (68-77°F) [See USP]. Discard the vial six (6) hours after reconstitution.
10. The patient dose should be measured by suitable radioactivity calibration system immediately prior to administration.

Blood Pool Imaging

The non-radioactive Kit for the Preparation of Technetium Tc 99m Pyrophosphate Injection is prepared by adhering to the following aseptic procedure:

1. Remove the white flip-off cap from the vial and swab the top of the vial closure with alcohol to sterilize the surface.
2. Reconstitute the reaction vial with 3 milliliters of sterile, non-pyrogenic, isotonic saline containing no preservatives.
3. Swirl the contents of the vial for one minute and let stand for at least 10 minutes.
4. Record date and time of preparation.
5. Examine vial contents for particulates and discoloration prior to injection.
6. Withdrawals for administration must be made aseptically using a sterile syringe and needle. Since the vials contain nitrogen to prevent oxidation of the complex, the vials should not be vented. If repeated withdrawals are made from a vial, the replacement of contents with air should be minimized.
7. Aseptically withdraw the reconstituted non-radioactive Kit for the Preparation of Technetium Tc 99m Pyrophosphate Injection with a sterile syringe for use within six (6) hours of preparation. For optimal results, this time should be minimized. The vial contains no bacteriostatic preservative. Store the reconstituted vial at 20-25°C (68-77°F) [See USP]. Discard the vial six (6) hours after reconstitution.
8. Between one-third and a total vial of stannous pyrophosphate may be administered by direct venipuncture 30 minutes prior to intravenous administration of 555 to 740 megabecquerels (15-20 mCi) of Sodium Pertechnetate Tc 99m Injection. Heparinized catheter systems should not be used.
9. The patient dose of Sodium Pertechnetate Tc 99m Injection should be measured by a suitable radioactivity calibration system immediately prior to administration.

NDC # 45567-0060-1 for 5 vial kits

NDC # 45567-0060-2 for 30 vial kits

This reagent kit for preparation of a radiopharmaceutical is approved for use by persons licensed pursuant to Section 120.547, Code of Massachusetts Regulation 105, or under equivalent license of the U.S. Nuclear Regulatory Commission or an Agreement State.

Manufactured By:

Sun Pharmaceutical Industries, Inc.

Billerica, MA 01821

PL-000017

Rev 2

Feb 2025

PACKAGE/LABEL PRINCIPAL DISPLAY PANEL- VIAL CONTAINER

STERILE NON-PYROGENIC DIAGNOSTIC MULTIDOSE

KIT FOR THE PREPARTION OF TECHNETIUM Tc 99m PYROPHOSPHATE INJECTION

Each 10mL reaction vial contains in 12.0 mg sodium pyrophosphate, 2.8 mg minimum stannous tin as stannous chloride dihydrate and 4.9 mg maximum total tin as stannous chloride dehydrate; pH is adjusted to 5.3-5.7 with HCI prior to lyophilization. Sealed under nitrogen. Refer to Package Insert for directions for use and the recommended adult doses.

Manufactured by:

Sun Pharmaceutical Industries, Inc.

Billerica, MA 01821

PL-000018

Rev 0.2

Mar 2020

CONTAINS NO BACTERIOSTATIC PRESERVATIVE. FOR INTRAVENOUS
USE ONLY AFTER RECONSTITION WITH LABELING OXIDANT-FREE
TECHENTIUM Tc 99m or ISOTONIC SALINE. . Store at 20-25°C (68-77°F)

[See USP] after reconstitution and use within 6 hours.

Rx Only

Package/Label Display Panel-5 VIAL BOX

Kit for the Preparation of Technetium Tc99m Pyrophosphate Injection

Manufactured By:

Sun Pharmaceutical Industries, Inc.

Billerica, MA 01821

For Customer Service call: 1-800-221-7554

CONTENTS:

1 package insert, 10 radiation labels and 5 reaction vials. Each 10 mL reaction vial contains 12.0 mg sodium pyrophosphate, 2.8 mg minimum stannous tin as stannous chloride dehydrate and 4.9 mg maximum total tin as stannous chloride deihydrate. pH is adjusted to 5.3 – 5.7 with HCI prior to lyophilization. Sealed under nitrogen. Contains no bacteriostatic preservative. For intravenous use only after reconstitution with oxidant-free Technetium Tc 99m or isotonic saline. Do not use if solution is cloudy.

STORE KIT AS PACKAGED AT 20-25°C (68-77°F) [SEE USP]

Store reconstituted vials at 20-25°C (68-77°F) [See USP]. Use within 6 hours after reconstitution. Refer to Package Insert for recommended adult doses.

IMPORTANT: Read enclosed Package Insert for full information on preparation, use and indications.

Manufactured By:

Sun Pharmaceutical Industries, Inc.

Billerica, MA 01821

For Customer Service call: 1-800-221-7554

PL-000020

Rev 0.3

Mar 2020

Package/Label Display Panel- Radiation Label

CAUTION RADIOACTIVE MATERIAL

STERILE, NON-PYROGENIC, DIAGNOSTIC, MULTIDOSE TECHNETIUM Tc 99m PYROPHOSPHATE INJECTION FOR INTRAVENOUS USE

Total MBq (mCi)_____Volume_____

Assay_____MBq/mL(mCi/mL) as of _____

Each 10mL reaction vial contains 12.0 mg sodium pyrophosphate, 2.8 mg minimum stannous tin as stannous chloride dihydrate and 4.9 mg maximum total tin as stannous chloride dihydrate; pH is adjusted to 5.3-5.7 with HCI prior to lyophilization. Sealed under nitrogen. Contains no bacteriostatic preservative. For intravenous use only after reconstitution with oxidant-free Technetium Tc 99m. Do not use if solution is cloudy. Store reconstituted vial at 20-25°C (68-77°F) [see USP]. Use within 6 hours after labeling with Technetium Tc 99m. Refer to Package Insert for recommended adult doses.

(SEE ENCLOSED PACKAGE INSERT)

RX ONLY

Manufactured By:

Sun Pharmaceutical Industries, Inc.

Billerica, MA 01821

PL-000019

Rev 0.2

Mar 2020

Package/Label Display Panel-30 Vial Box

Kit for the preparation of Technetium Tc99m Pyrophosphate Injection

STERILE, NON-PYROGENIC, DIAGNOSTIC, MULTIDOSE

Rx only.

Manufactured By:

Sun Pharmaceutical Industries, Inc.

Billerica, MA 01821

For Customer Service call: 1-800-221-7554

Sterile Diagnostic Multidose Non-Pyrogenic

CONTENTS: 1 Package insert, 60 radiation labels and 30 reaction vials. Each 10 mL vial contains 12.0 mg sodium pyrophosphate, 2.8 mg minimum stannous tin as stannous chloride dihydrate and 4.9 mg maximum total tin as stannous chloride dihydrate. pH is adjusted to 5.3 – 5.7 with HCI prior to lyophilization. Sealed under nitrogen. Contains no bacteriostatic preservative. For intravenous use only after reconstitution with oxidant-free Technetium Tc 99m or isotonic saline. Do not use if solution is cloudy.

Store the kit as packaged AT 20-25°C (68-77°F) [See USP]

Store reconstituted vials at 20-25°C (68-77°F) [See USP]. Use within 6 hours after reconstitution.

Refer to Package Insert for recommended adult doses.

IMPORTANT: Read enclosed Package Insert for full information on preparation, use and indications.

Manufactured By:

Sun Pharmaceutical Industries, Inc.

Billerica, MA 01821

PL-000021

Rev 0.3

Mar 2020